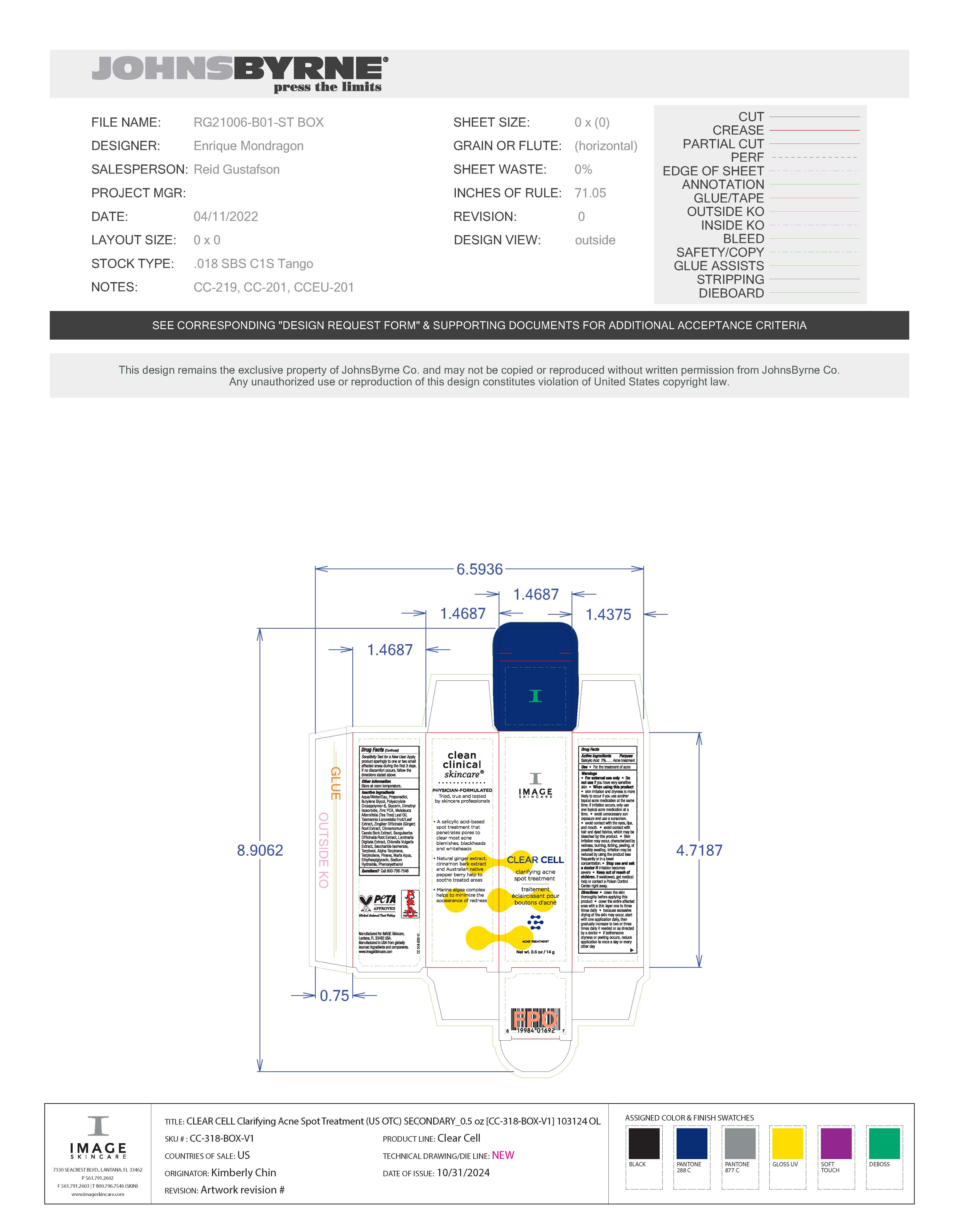 DRUG LABEL: Image Clear Cell Acne Spot Treatment
NDC: 60232-5022 | Form: GEL
Manufacturer: Swiss-American CDMO, LLC
Category: otc | Type: HUMAN OTC DRUG LABEL
Date: 20251211

ACTIVE INGREDIENTS: SALICYLIC ACID 20 g/1000 g
INACTIVE INGREDIENTS: WATER; DIMETHYL ISOSORBIDE; PROPANEDIOL; BUTYLENE GLYCOL; SODIUM HYDROXIDE; SODIUM CHLORIDE; SODIUM CARBONATE; GLYCERIN; TASMANNIA LANCEOLATA FRUIT; CINNAMOMUM CASSIA BARK; ZINGIBER OFFICINALE (GINGER) ROOT OIL; SANGUISORBA OFFICINALIS ROOT; LAMINARIA DIGITATA; CHLORELLA VULGARIS; SACCHARIDE ISOMERATE; PHENOXYETHANOL; ETHYLHEXYLGLYCERIN; ZINC PCA; MELALEUCA ALTERNIFOLIA (TEA TREE) LEAF OIL; POLYACRYLATE CROSSPOLYMER-6

Image Skincare Clear Cell Acne Spot Treatment

Warnings

For external use only. Do not use if you have very sensitive skin. When using this product, skin irritation and dryness is more likely to occur if you use another topical acne medication at the same time. If irritation occurs, only use one topical acne medication at a time. Avoid unnecessary sun exposure and use a sunscreen. Avoid contact with the eyes, lips and mouth. Avoid contact with hair and dyed fabrics, which may be bleached by this product. Skin irritation may occur, characterized by redness, burning, itching, peeling, or possibly swelling. Irritation may be reduced by using the product less frequently or in a lower concentration. Stop use and ask a doctor if irritation becomes severe. If swallowed, get medical help or contact a Poison Control Center right away.

Active Ingredients

Salicylic Acid 2%

Purpose

Acne treatment

Use

For the treatment of acne

Directions

Clean the skin thoroughly before applying this product. Cover the entire affected area with a thin layer one to three times daily. Because excessive drying of the skin may occur, start with one application daily, then gradually increase to two or three times daily if needed or as directed by a doctor. If bothersome dryness or peelig occurs, reduce application to once a day or every other day.

Sensitivity Test for a New User: Apply product sparingly to one or two small affected areas during the first 3 days. If no discomfort occurs, follow the directions stated above.

Keep out of reach of children

Other information

Store at room temperature

Inactive Ingredients

water, propanediol, butylene glycol, polyacrylate crosspolymer-6, glycerin, dimethyl isosorbide, zinc PCA, melaleuca alfernifolia (tea tree) leaf oil, tasmannia lanceolata fruit/leaf extract, zingiber officinale (ginger) root extract, cinnamomum cassia bark extract, sanguisorba officinalis root extract, laminaria digitata extract, chlorella vulgaris extract, saccharide isomerate, terpineol, alpha-terpinene, trpinolene, pinene, maris aqua, ethylhexylgylcerin, sodium hdyroxide, phenoxyethanol

Questions

Questions? Call 800-796-7546